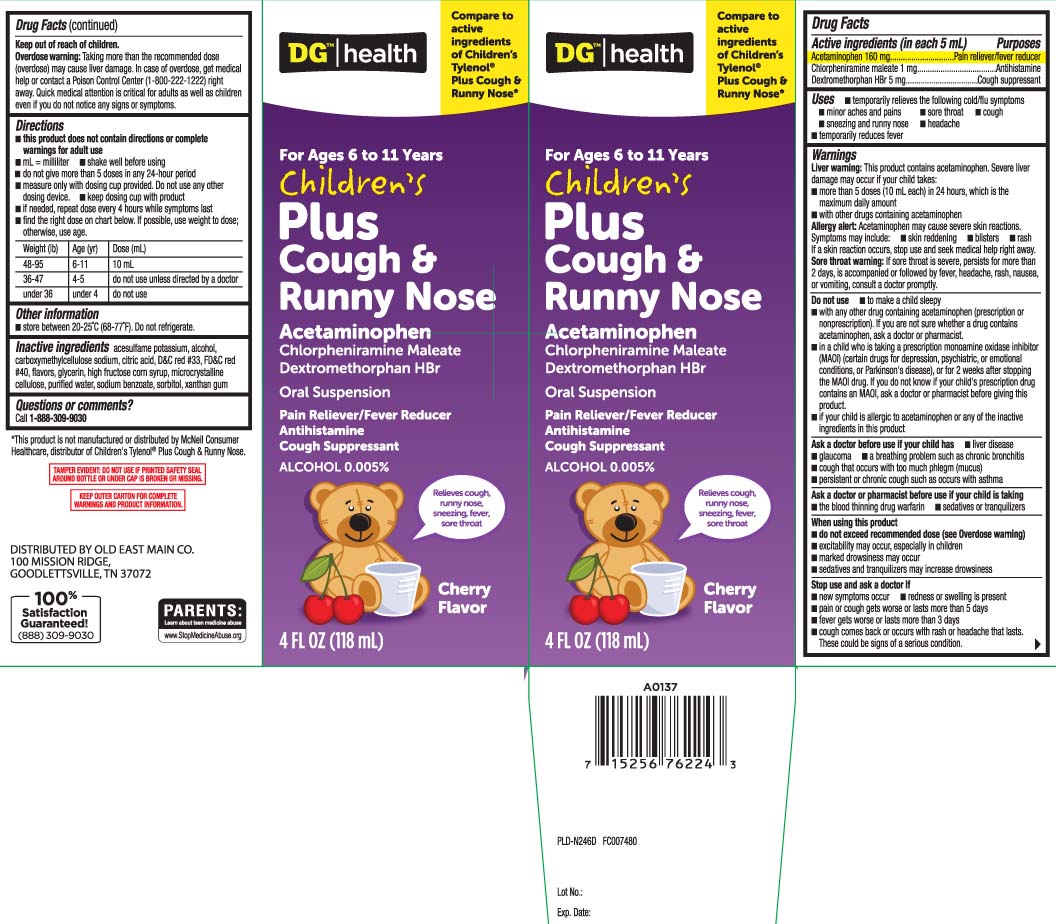 DRUG LABEL: Childrens Plus Cough and Runny Nose
NDC: 55910-297 | Form: SUSPENSION
Manufacturer: Dolgencorp, Inc.  (DOLLAR GENERAL & REXALL)
Category: otc | Type: HUMAN OTC DRUG LABEL
Date: 20241014

ACTIVE INGREDIENTS: ACETAMINOPHEN 160 mg/5 mL; CHLORPHENIRAMINE MALEATE 1 mg/5 mL; DEXTROMETHORPHAN HYDROBROMIDE 5 mg/5 mL
INACTIVE INGREDIENTS: ACESULFAME POTASSIUM; CARBOXYMETHYLCELLULOSE SODIUM; CELLULOSE, MICROCRYSTALLINE; ANHYDROUS CITRIC ACID; GLYCERIN; HIGH FRUCTOSE CORN SYRUP; WATER; D&C RED NO. 33; FD&C RED NO. 40; SODIUM BENZOATE; SORBITOL; XANTHAN GUM; ALCOHOL

Drug Facts

Active ingredients (in each 5 mL)

Acetaminophen 160 mg

Chlorpheniramine maleate 1 mg

Dextromethorphan HBr 5 mg

Purposes

Pain reliever/fever reducer

Antihistamine

Cough suppressant

Uses

- temporarily relieves the following cold/flu symptoms:
  - minor aches and pains
  - sore throat
  - cough
  - sneezing and runny nose
  - headache
- temporarily reduces fever

Warnings

Liver warning: This product contains acetaminophen. Severe liver damage may occur if your child takes:

- more than 5 doses (10 mL) in 24 hours, which is the maximum daily amount
- with other drugs contaning acetaminophen

Allergy alert: Acetaminophen may cause severe skin reactions. Symptoms may include:

- skin reddening
- blisters
- rash

If a skin reaction occurs, stop use and seek medical help right away.

Sore throat warning: If sore throat is severe, persists for more than 2 days, is accompanied or followed by fever, headache, rash, nausea, or vomiting, consult a doctor promptly.

Do not use

- to make a child sleepy
- in a child who is taking a prescription monoamine oxidase inhibitor (MAOI) (certain drugs for depression, psychiatric or emotional conditions, or Parkinson’s disease), or for 2 weeks after stopping the MAOI drug. If you do not know if your child's prescription drug contains an MAOI, ask a doctor or pharmacist before giving this product.
- with any other drug containing acetaminophen (prescription or non-prescription). If you are not sure whether a drug contains acetaminophen, ask a doctor or pharmacist.
- if your child is allergic to acetaminophen or any of the inactive ingredients in this product.

Ask a doctor before use if the child has

- liver disease
- glaucoma
- a breathing problem such as chronic bronchitis
- cough that occurs with too much phlegm (mucus)
- persistent or chronic cough such as occurs with asthma

Ask a doctor or pharmacist before use if the child is taking

- sedatives or tranquilizers
- the blood thinning drug warfarin

When using this product

- do not exceed recommended dose (see overdose warning)
- excitability may occur, especially in children
- marked drowsiness may occur
- sedatives and tranquilizers may increase drowsiness

Stop use and ask a doctor if

- new symptoms occur
- redness or swelling is present
- pain or cough gets worse or lasts for more than 5 days
- fever gets worse or lasts more than 3 days
- cough comes back or occurs with rash or headache that lasts

These could be signs of a serious condition.

Keep out of reach of children.

Overdose warning: Taking more than the recommended dose (overdose) may cause liver damage. In case of overdose, get medical help or contact a Poison Control Center (1-800-222-1222) right away. Quick medical attention is critical for adults as well as children even if you do not notice any signs or symptoms.

Directions

- this product does not contain directions or complete warnings for adult use.
- mL = milliliter
- shake well before using
- do not give more than 5 doses in any 24-hour period
- measure only with dosing cup provided. Do not use any other dosing device.
- keep dosing cup with product
- if needed, repeat dose every 4 hours while symptoms last
- find the right dose on chart below. If possible, use weight to dose; otherwise, use age

Weight (lb) | Age (yr) | Dose (mL)
48-95 | 6-11 | 10 mL
36-47 | 4-5 | do not use unless directed by a doctor
under 36 | under 4 | do not use

Other Information

- store between 20-25ºC (68-77ºF). Do not refrigerate.

Inactive ingredients

acesulfame potassium, alcohol, carboxymethylcellulose sodium, citric acid, D&C red #33, FD&C red #40, flavors, glycerin, high fructose corn syrup, microcrystalline cellulose purified water, sodium benzoate, sorbitol, xanthan gum

Questions or comments?

Call 1-888-309-9030

Principal Display Panel

Compare to active ingredients of Children's Tylenol® Plus Cough & Runny Nose*

For Ages 6 to 11 Years

Children's

Plus Cough & Runny Nose

Acetaminophen

Chlorpheniramine maleate

Dextromethorphan HBr

Oral Suspension

Pain reliever/fever reducer

Antihistamine

Cough suppressant

ALCOHOL 0.02%

Relieves cough, runny nose, sneezing, fever, sore throat

Cherry Flavor

FL OZ (mL)

Dosage Cup Provided

*This product is not manufactured or distributed by McNeil Consumer Healthcare,distributor of Children's Tylenol® Plus Cough & Runny Nose.

TAMPER EVIDENT: DO NOT USE IF PRINTED SAFETY SEAL AROUND BOTTLE OR UNDER CAP IS BROKEN OR MISSING.

KEEP OUTER CARTON FOR COMPLETE WARNINGS AND PRODUCT INFORMATION.

DISTRIBUTED BY OLD EAST MAIN CO.

100 MISSION RIDGE

GOODLETTSVILLE, TN 37072

Package Label

DOLLAR GENERAL HEALTH Children's Plus Cough & Runny Nose